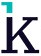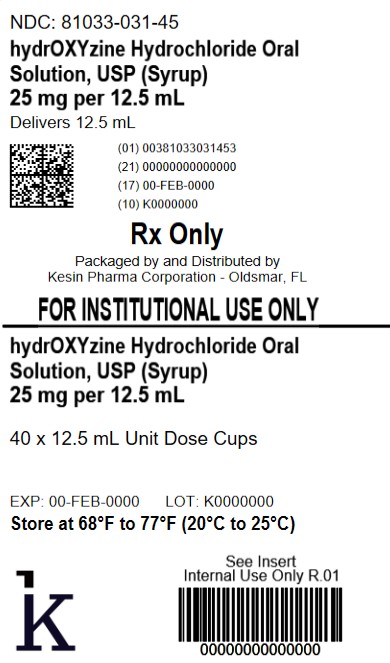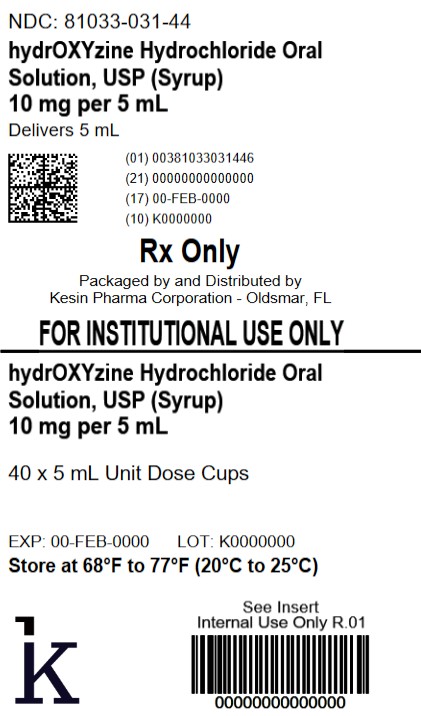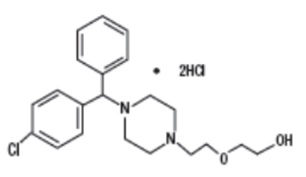 DRUG LABEL: Hydroxyzine Hydrochloride
NDC: 81033-031 | Form: SOLUTION
Manufacturer: Kesin Pharma
Category: prescription | Type: HUMAN PRESCRIPTION DRUG LABEL
Date: 20260227

ACTIVE INGREDIENTS: HYDROXYZINE DIHYDROCHLORIDE 10 mg/5 mL
INACTIVE INGREDIENTS: ANHYDROUS CITRIC ACID; SODIUM BENZOATE; SUCROSE; WATER

hydrOXYzine Hydrochloride Oral Solution, USP (Syrup)
Rx only

DESCRIPTION

Hydroxyzine hydrochloride, USP is designated chemically as (±)-2-[2-[4-(p-Chloro-α-phenylbenzyl)-1-piperazinyl]ethoxy]ethanol dihydrochloride. Its structural formula is as follows:

C21H27ClN2O2•2HCl M.W. 447.83 g/mol

Inactive ingredientsfor hydroxyzine hydrochloride oral solution, USP are: flavadew coolmint flavour; sodium benzoate; sucrose; and purified water. Anhydrous citric acid is used for pH adjustment. The pH range is between 2.0 and 4.3.

CLINICAL PHARMACOLOGY

Hydroxyzine hydrochloride is unrelated chemically to the phenothiazines, reserpine, meprobamate, or the benzodiazepines.

Hydroxyzine is not a cortical depressant, but its action may be due to suppression of activity in certain key regions of the subcortical area of the central nervous system.

Primary skeletal muscle relaxation has been demonstrated experimentally. Bronchodilator activity, and antihistaminic and analgesic effects have been demonstrated experimentally and confirmed clinically. An antiemetic effect, both by the apomorphine test and the veriloid test, has been demonstrated. Pharmacological and clinical studies indicate that hydroxyzine in therapeutic dosage does not increase gastric secretion or acidity and in most cases has mild antisecretory activity.

Hydroxyzine is rapidly absorbed from the gastrointestinal tract and its clinical effects are usually noted within 15 minutes to 30 minutes after oral administration.

INDICATIONS AND USAGE

For symptomatic relief of anxiety and tension associated with psychoneurosis and as an adjunct in organic disease states in which anxiety is manifested.

Useful in the management of pruritus due to allergic conditions such as chronic urticaria and atopic and contact dermatoses, and in histamine-mediated pruritus.

As a sedative when used as premedication and following general anesthesia, hydroxyzine may potentiate meperidineand barbiturates,so their use in pre-anesthetic adjunctive therapy should be modified on an individual basis. Atropine and other belladonna alkaloids are not affected by the drug. Hydroxyzine is not known to interfere with the action of digitalis in any way and it may be used concurrently with this agent.

The effectiveness of hydroxyzine as an antianxiety agent for long term use, that is more than 4 months, has not been assessed by systematic clinical studies. The physician should reassess periodically the usefulness of the drug for the individual patient.

CONTRAINDICATIONS

Oral hydroxyzine hydrochloride is contraindicated in patients with known hypersensitivity to hydroxyzine hydrochloride products, and in patients with known hypersensitivity to cetirizine hydrochloride or levocetirizine hydrochloride.

Hydroxyzine is contraindicated in patients with a prolonged QT interval.

Hydroxyzine, when administered to the pregnant mouse, rat and rabbit, induced fetal abnormalities in the rat and mouse at doses substantially above the human therapeutic range. Clinical data in human beings are inadequate to establish safety in early pregnancy. Until such data are available, hydroxyzine is contraindicated in early pregnancy.

Hydroxyzine is contraindicated for patients who have shown a previous hypersensitivity to it.

WARNINGS

Keep out of the reach of children.

Nursing Mothers

It is not known whether this drug is excreted in human milk. Since many drugs are so excreted, hydroxyzine should not be given to nursing mothers.

PRECAUTIONS

THE POTENTIATING ACTION OF HYDROXYZINE MUST BE CONSIDERED WHEN THE DRUG IS USED IN CONJUNCTION WITH CENTRAL NERVOUS SYSTEM DEPRESSANTS SUCH AS NARCOTICS, NON-NARCOTIC ANALGESICS AND BARBITURATES.Therefore, when central nervous system depressants are administered concomitantly with hydroxyzine, their dosage should be reduced.

QT Prolongation/Torsade de Pointes (TdP)

Cases of QT prolongation and Torsade de Pointes have been reported during post-marketing use of hydroxyzine. The majority of reports occurred in patients with other risk factors for QT prolongation/TdP (preexisting heart disease, electrolyte imbalances or concomitant arrhythmogenic drug use). Therefore, hydroxyzine should be used with caution in patients with risk factors for QT prolongation, congenital long QT syndrome, a family history of long QT syndrome, other conditions that predispose to QT prolongation and ventricular arrhythmia, as well as recent myocardial infarction, uncompensated heart failure, and bradyarrhythmias.

Caution is recommended during the concomitant use of drugs known to prolong the QT interval. These include Class 1A (e.g., quinidine, procainamide) or Class III (e.g., amiodarone, sotalol) antiarrhythmics, certain antipsychotics (e.g., ziprasidone, iloperidone, clozapine, quetiapine, chlorpromazine), certain antidepressants (e.g., citalopram, fluoxetine), certain antibiotics (e.g., azithromycin, erythromycin, clarithromycin, gatifloxacin, moxifloxacin); and others (e.g., pentamidine, methadone, ondansetron, droperidol).

Since drowsiness may occur with use of this drug, patients should be warned of this possibility and cautioned against driving a car or operating dangerous machinery while taking hydroxyzine. Patients should be advised against the simultaneous use of other CNS depressant drugs, and cautioned that the effect of alcohol may be increased.

Geriatric Use

A determination has not been made whether controlled clinical studies of hydroxyzine included sufficient numbers of subjects aged 65 and over to define a difference in response from younger subjects. Other reported clinical experience has not identified differences in responses between the elderly and younger patients. In general, dose selection for an elderly patient should be cautious, usually starting at the low end of the dosing range, reflecting the greater frequency of decreased hepatic, renal or cardiac function, and of concomitant disease or other drug therapy.

The extent of renal excretion of hydroxyzine has not been determined. Because elderly patients are more likely to have decreased renal function, care should be taken in dose selections.

Sedating drugs may cause confusion and over sedation in the elderly; elderly patients generally should be started on low doses of hydroxyzine and observed closely.

Acute Generalized Exanthematous Pustulos is (AGEP)

Hydroxyzine may rarely cause acute generalized exanthematous pustulosis (AGEP), a serious skin reaction characterized by fever and numerous small, superficial, non-follicular, sterile pustules, arising within large areas of edematous erythema. Inform patients about the signs of AGEP, and discontinue hydroxyzine at the first appearance of a skin rash, worsening of pre-existing skin reactions which hydroxyzine may be used to treat, or any other sign of hypersensitivity. If signs or symptoms suggest AGEP, use of hydroxyzine should not be resumed and alternative therapy should be considered. Avoid cetirizine or levocetirizine in patients who have experienced AGEP or other hypersensitivity reactions with hydroxyzine, due to the risk of cross-sensitivity.

ADVERSE REACTIONS

Side effects reported with the administration of hydroxyzine hydrochloride are usually mild and transitory in nature.

Skin and appendages: Oral hydroxyzine hydrochloride is associated with Acute Generalized Exanthematous Pustulosis (AGEP), fixed drug eruptions, pruritis, rash and urticaria in post marketing reports.

Anticholinergic: Dry mouth.

Central Nervous System: Drowsiness is usually transitory and may disappear in a few days of continued therapy or upon reduction of the dose. Involuntary motor activity including rare instances of tremor and convulsions have been reported, usually with doses considerably higher than those recommended. Clinically significant respiratory depression has not been reported at recommended doses.

Cardiac System: QT prolongation, Torsade de Pointes.

To report SUSPECTED ADVERSE REACTIONS, contact Kesin Pharma at 1-833-537-4679 or FDA at 1-800-FDA-1088 or www.fda.gov/medwatch.

OVERDOSAGE

The most common manifestation of hydroxyzine overdosage is hypersedation. As in the management of overdosage with any drug, it should be borne in mind that multiple agents may have been taken.

If vomiting has not occurred spontaneously, it should be induced. Immediate gastric lavage is also recommended. General supportive care, including frequent monitoring of the vital signs and close observation of the patient, is indicated. Hypotension, though unlikely, may be controlled with intravenous fluids and levarterenol, or metaraminol. Do not use epinephrine as hydroxyzine counteracts its pressor action.

Hydroxyzine overdose may cause QT prolongation and Torsade de Pointes. ECG monitoring is recommended in cases of hydroxyzine overdose.

There is no specific antidote. It is doubtful that hemodialysis would be of any value in the treatment of overdosage with hydroxyzine. However, if other agents such as barbiturates have been ingested concomitantly, hemodialysis may be indicated. There is no practical method to quantitate hydroxyzine in body fluids or tissue after its ingestion or administration.

DOSAGE AND ADMINISTRATION

For symptomatic relief of anxiety and tension associated with psychoneurosis and as an adjunct in organic disease states in which anxiety is manifested: in adults, 50 mg to 100 mg four times daily; children under 6 years, 50 mg daily in divided doses and children over 6 years, 50 mg to 100 mg daily in divided doses.

For use in the management of pruritus due to allergic conditions such as chronic urticaria and atopic and contact dermatoses, and in histamine-mediated pruritus: in adults, 25 mg three times to four times daily; children under 6 years, 50 mg daily in divided doses and children over 6 years, 50 mg to 100 mg daily in divided doses.

As a sedative when used as a premedication and following general anesthesia: 50 mg to 100 mg in adults, and 0.6 mg/kg in children.

When treatment is initiated by the intramuscular route of administration, subsequent doses may be administered orally.

As with all medications, the dosage should be adjusted according to the patient’s response to therapy.

HOW SUPPLIED

Hydroxyzine hydrochloride oral solution, USP (Syrup) 10 mg per 5 mL (teaspoonful) is a clear colourless, flavadew coolmint flavoured liquid, supplied in the following:
NDC 81033-031-05: 5 mL unit-dose cup
NDC 81033-031-12: 12.5 mL unit-dose cup
NDC 81033-031-44: Carton containing 40 unit-dose cups of 5 mL each
NDC 81033-031-45: Carton containing 40 unit-dose cups of 12.5 mL each

RECOMMENDED STORAGE

Store at 20°C to 25°C (68°F to 77°F); excursions permitted to 15°C to 30°C (59°F to 86°F) [See USP Controlled Room Temperature].
PROTECT FROM FREEZING
PROTECT FROM LIGHT

Distributed by:
Kesin Pharma
Oldsmar, FL 34677
Rev. 02/2026
PI-031-V01

PACKAGE LABEL

NDC 81033-031-44

hydrOXYzine Hydrochloride Oral Solution, USP (Syrup)

10 mg per 5 mL

Rx Only

40 x 5 mL Unit Dose Cups

PACKAGE LABEL

NDC 81033-031-44

hydrOXYzine Hydrochloride Oral Solution, USP

25 mg per 12.5 mL

Rx Only

40 x 12.5 mL Units Dose Cups